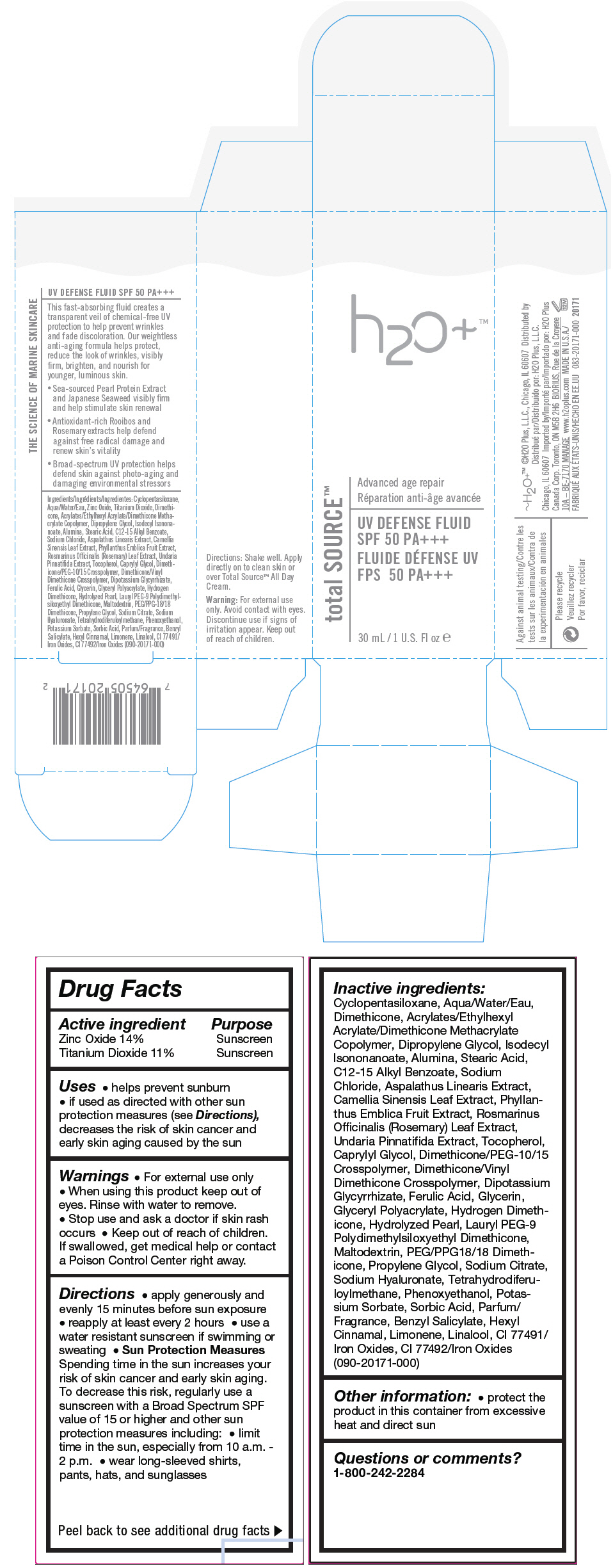 DRUG LABEL: UV Defense Fluid
NDC: 65903-171 | Form: CREAM
Manufacturer: H2O Plus
Category: otc | Type: HUMAN OTC DRUG LABEL
Date: 20140414

ACTIVE INGREDIENTS: Titanium Dioxide 11 g/100 mL; Zinc Oxide 14 g/100 mL
INACTIVE INGREDIENTS: Aluminum Oxide; Water; Alkyl (C12-15) Benzoate; Green Tea Leaf; Caprylyl Glycol; Cyclomethicone 5; Dimethicone; Dimethicone/Vinyl Dimethicone Crosspolymer (Hard Particle); Glycyrrhizinate Dipotassium; Dipropylene Glycol; Ferulic Acid; Glycerin; Calcium Carbonate; Ferric Oxide Red; Isodecyl Isononanoate; Lauryl PEG-9 Polydimethylsiloxyethyl Dimethicone; Maltodextrin; PEG/PPG-18/18 Dimethicone; Phenoxyethanol; Phyllanthus Emblica Fruit; Potassium Sorbate; Propylene Glycol; Rosemary; Sodium Chloride; Sodium Citrate; Hyaluronate Sodium; Sorbic Acid; Stearic Acid; Tetrahydrodiferuloylmethane; Tocopherol; Undaria Pinnatifida; Benzyl Benzoate; .Alpha.-Hexylcinnamaldehyde; Limonene, (-)-; Linalool, (+/-)-

UV Defense Fluid

Drug Facts

ACTIVE INGREDIENT

Active ingredient | Purpose
Zinc Oxide 14% | Sunscreen
Titanium Dioxide 11% | Sunscreen

Uses

- helps prevent sunburn
- if used as directed with other sun protection measures (see Directions), decreases the risk of skin cancer and early skin aging caused by the sun

Warnings

- For external use only

- When using this product keep out of eyes. Rinse with water to remove.

- Stop use and ask a doctor if skin rash occurs

- Keep out of reach of children. If swallowed, get medical help or contact a Poison Control Center right away.

Directions

- apply generously and evenly 15 minutes before sun exposure
- reapply at least every 2 hours
- use a water resistant sunscreen if swimming or sweating
- Sun Protection Measures Spending time in the sun increases your risk of skin cancer and early skin aging. To decrease this risk, regularly use a sunscreen with a Broad Spectrum SPF value of 15 or higher and other sun protection measures including:
  - limit time in the sun, especially from 10 a.m. - 2 p.m.
  - wear long-sleeved shirts, pants, hats, and sunglasses

Inactive ingredients

Cyclopentasiloxane, Aqua/Water/Eau, Dimethicone, Acrylates/Ethylhexyl Acrylate/Dimethicone Methacrylate Copolymer, Dipropylene Glycol, Isodecyl Isononanoate, Alumina, Stearic Acid, C12-15 Alkyl Benzoate, Sodium Chloride, Aspalathus Linearis Extract, Camellia Sinensis Leaf Extract, Phyllanthus Emblica Fruit Extract, Rosmarinus Officinalis (Rosemary) Leaf Extract, Undaria Pinnatifida Extract, Tocopherol, Caprylyl Glycol, Dimethicone/PEG-10/15 Crosspolymer, Dimethicone/Vinyl Dimethicone Crosspolymer, Dipotassium Glycyrrhizate, Ferulic Acid, Glycerin, Glyceryl Polyacrylate, Hydrogen Dimethicone, Hydrolyzed Pearl, Lauryl PEG-9 Polydimethylsiloxyethyl Dimethicone, Maltodextrin, PEG/PPG18/18 Dimethicone, Propylene Glycol, Sodium Citrate, Sodium Hyaluronate, Tetrahydrodiferuloylmethane, Phenoxyethanol, Potassium Sorbate, Sorbic Acid, Parfum/ Fragrance, Benzyl Salicylate, Hexyl Cinnamal, Limonene, Linalool, CI 77491/ Iron Oxides, CI 77492/Iron Oxides (090-20171-000)

Other information

- protect the product in this container from excessive heat and direct sun

Questions or comments?

1-800-242-2284

Distributed by:
H2O Plus, L.L.C.
Chicago, IL 60607

PRINCIPAL DISPLAY PANEL - 30 mL Bottle Carton

h2o+™

total SOURCE™

Advanced age repair

UV DEFENSE FLUID
SPF 50 PA+++

30 mL / 1 U.S. Fl oz e